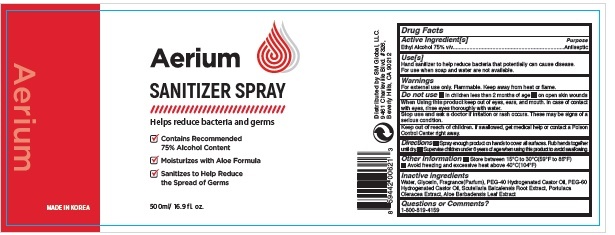 DRUG LABEL: Aerium Sanitizer 75% 500ml
NDC: 74924-110 | Form: SPRAY
Manufacturer: SM Global, LLC.
Category: otc | Type: HUMAN OTC DRUG LABEL
Date: 20200605

ACTIVE INGREDIENTS: ALCOHOL 75 mL/100 mL
INACTIVE INGREDIENTS: PEG-60 HYDROGENATED CASTOR OIL; SCUTELLARIA BAICALENSIS ROOT; PURSLANE; ALOE VERA LEAF; GLYCERIN; POLYOXYL 40 HYDROGENATED CASTOR OIL; WATER

Aerium Sanitizer Spray 75% 500ml

Active Ingredient(s)

Alcohol 80% v/v. Purpose: Antiseptic

Purpose

Antiseptic, Hand Sanitizer

Use

Hand Sanitizer to help reduce bacteria that potentially can cause disease. For use when soap and water are not available.

Warnings

For external use only. Flammable. Keep away from heat or flame

Do not use

- in children less than 2 months of age
- on open skin wounds

When using this product keep out of eyes, ears, and mouth. In case of contact with eyes, rinse eyes thoroughly with water.

Stop use and ask a doctor if irritation or rash occurs. These may be signs of a serious condition.

Keep out of reach of children. If swallowed, get medical help or contact a Poison Control Center right away.

Directions

- Spray enough product on hands to cover all surfaces. Rub hands together until dry.
- Supervise children under 6 years of age when using this product to avoid swallowing.

Other information

- Store between 15-30C (59-86F)
- Avoid freezing and excessive heat above 40C (104F)

Inactive ingredients

Water, Glycerin, Fragrance(Parfum), PEG-40 Hydrogenated Castor Oil, PEG-60 Hydrogenated Castor Oil, Scutellaria Baicalensis Root Extract, Portulaca Oleracea Extract, Aloe Barbadensis Leaf Extract

Package Label - Principal Display Panel

Aerium
Sanitizer Spray
Helps reduce bacteria and germs

- Contains Recommended 70% Alcohol Content
- Moisturizes with Aloe Formula
- Sanitizes to Help Reduce the Spread of Germs

500ml/ 16.9 fl.oz.